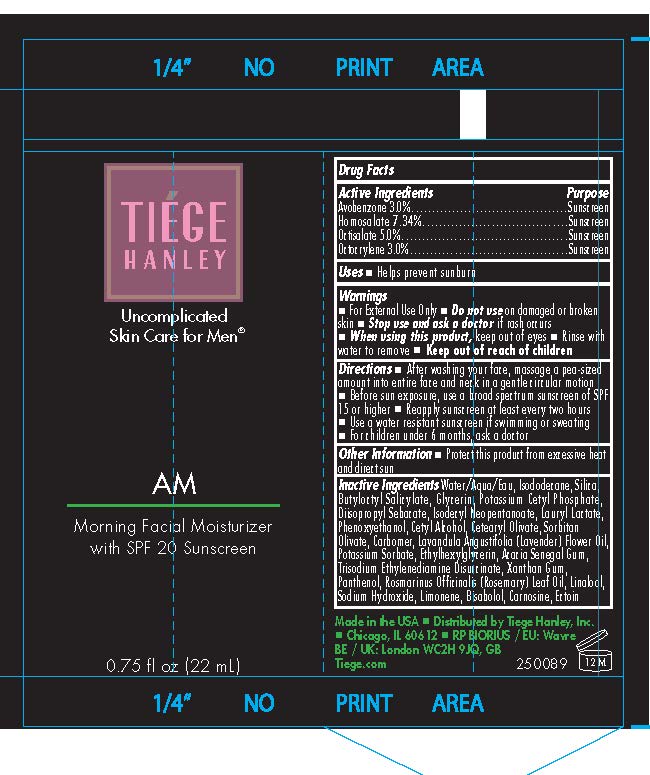 DRUG LABEL: Tiege Hanley AM Morning Facial Moisturizer with SPF 20
NDC: 71714-008 | Form: LOTION
Manufacturer: TIEGE HANLEY, Inc
Category: otc | Type: HUMAN OTC DRUG LABEL
Date: 20260223

ACTIVE INGREDIENTS: OCTISALATE 50 mg/1 mL; OCTOCRYLENE 30 mg/1 mL; AVOBENZONE 30 mg/1 mL; HOMOSALATE 73.4 mg/1 mL
INACTIVE INGREDIENTS: BISABOLOL; ISODODECANE; ROSEMARY OIL; ETHYLHEXYLGLYCERIN; GLYCERIN; WATER; BUTYLOCTYL SALICYLATE; LAVENDER OIL; ISODECYL NEOPENTANOATE; POTASSIUM CETYL PHOSPHATE; CARBOMER 940; LAURYL LACTATE; CETYL ALCOHOL; PHENOXYETHANOL; CETEARYL OLIVATE; SODIUM HYDROXIDE; SORBITAN OLIVATE; DIISOPROPYL SEBACATE; ACACIA SENEGAL GUM; LIMONENE, (+)-; PANTHENOL; XANTHAN GUM; POTASSIUM SORBATE; LINALOOL; SILICON DIOXIDE; TRISODIUM ETHYLENEDIAMINE DISUCCINATE; ECTOIN; CARNOSINE

Tiege Hanley AM Morning Facial Moisturizer with SPF 20
0.75 FL OZ (22ml) & 2.5 FL OZ (75 ml)

Active Ingredients

Avobenzene 3%

Homosalate 7.34%

Octisalate 5.0%

Octocrylene 3.0%

PURPOSE

SUNSCREEN

■ Keep out of reach of children

Warnings
■ For External Use Only
■ Do not use on damaged or broken skin
■ Stop use and ask a doctor if rash occurs
■ When using this product, keep out of eyes
■ Rinse with water to remove
■ Keep out of reach of children

Directions
■ After washing your face, massage a pea-sized
amount into entire face and neck in a gentle circular motion
■ Before sun exposure, use a broad-spectrum sunscreen of SPF
15 or higher
■ Reapply sunscreen at least every two hours
■ Use a water-resistant sunscreen if swimming or sweating
■ For children under 6 months, ask a doctor

INDICATIONS AND USAGE

Uses ■ Helps prevent sunburn

Inactive Ingredients
Water

Isododecane

Silica (silicone Dioxide)
Butyloctyl Salicylate

Glycerin
Potassium Cetyl Phosphate

Diisopropyl Sebacate

Isodecyl Neopentanoate

Lauryl Lactate

Phenoxyethanol
Cetyl Alcohol

Cetearyl Olivate

Sorbitan Olivate
Lavandula Angustifolia (Lavender) Flower Oil

Carbomer
Rosmarinus Officinalis (Rosemary) Leaf Oil

Potassium Sorbate
Ethylhexylglycerin

Acacia Senegal Gum
Trisodium Ethylenediamine Disuccinate

Xanthan Gum
Panthenol

Linalool
Sodium Hydroxide

Limonene

Bisabolol

Carnosine
Ectoin